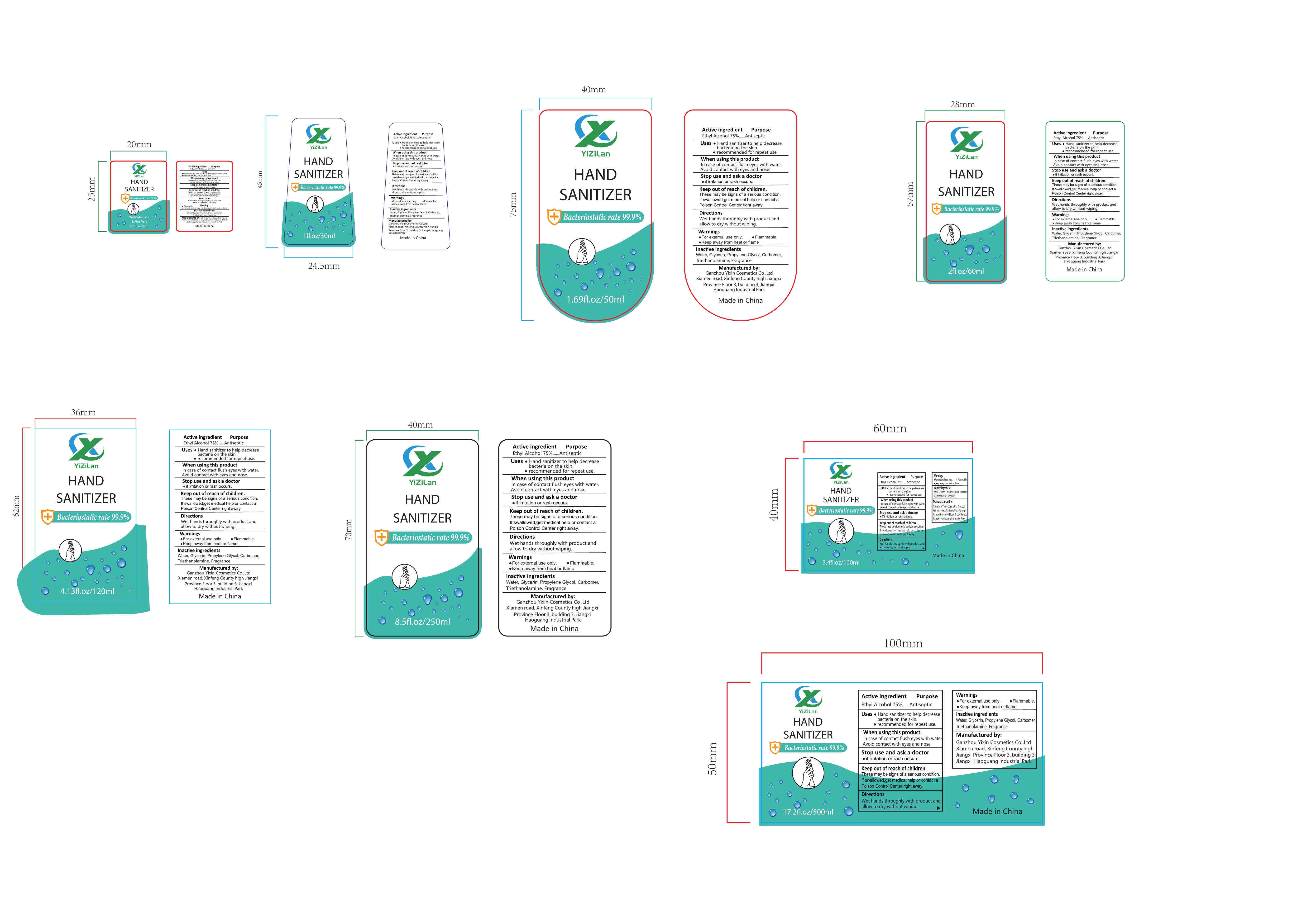 DRUG LABEL: Hand Sanitizer
NDC: 78496-006 | Form: GEL
Manufacturer: Ganzhou Yixin Cosmetics Co ,Ltd
Category: otc | Type: HUMAN OTC DRUG LABEL
Date: 20200604

ACTIVE INGREDIENTS: ALCOHOL 75 mL/100 mL
INACTIVE INGREDIENTS: TROLAMINE; GLYCERIN; CARBOMER HOMOPOLYMER TYPE B (ALLYL SUCROSE CROSSLINKED); WATER; PROPYLENE GLYCOL

Active Ingredient(s)

Ethyl Alcohol 75% v/v. Purpose: Antiseptic

Purpose

Antiseptic, Hand Sanitizer

Use

Hand sanitizer to help decreasebacteria on the skine recommended for repeat use

Warnings

For extemal use only. .Flammable,.Keep away from heat or flame

Do not use

/

WHEN USING

In case of contact flush eyes with water.Avoid contact with eyes and nose

Stop use and ask a doctorif irritation or rash occurs

Keep out of reach of children.These may be signs of a serious conditionIf swallowed, get medical help or contact a Poison Control Center right away.

Directions

Wet hands throughly with product and allow to dry without wiping

Other information

- /

Inactive ingredients

Water, Glycerin, Propylene Glycol, CarbomerTriethanolamine, Fragrance